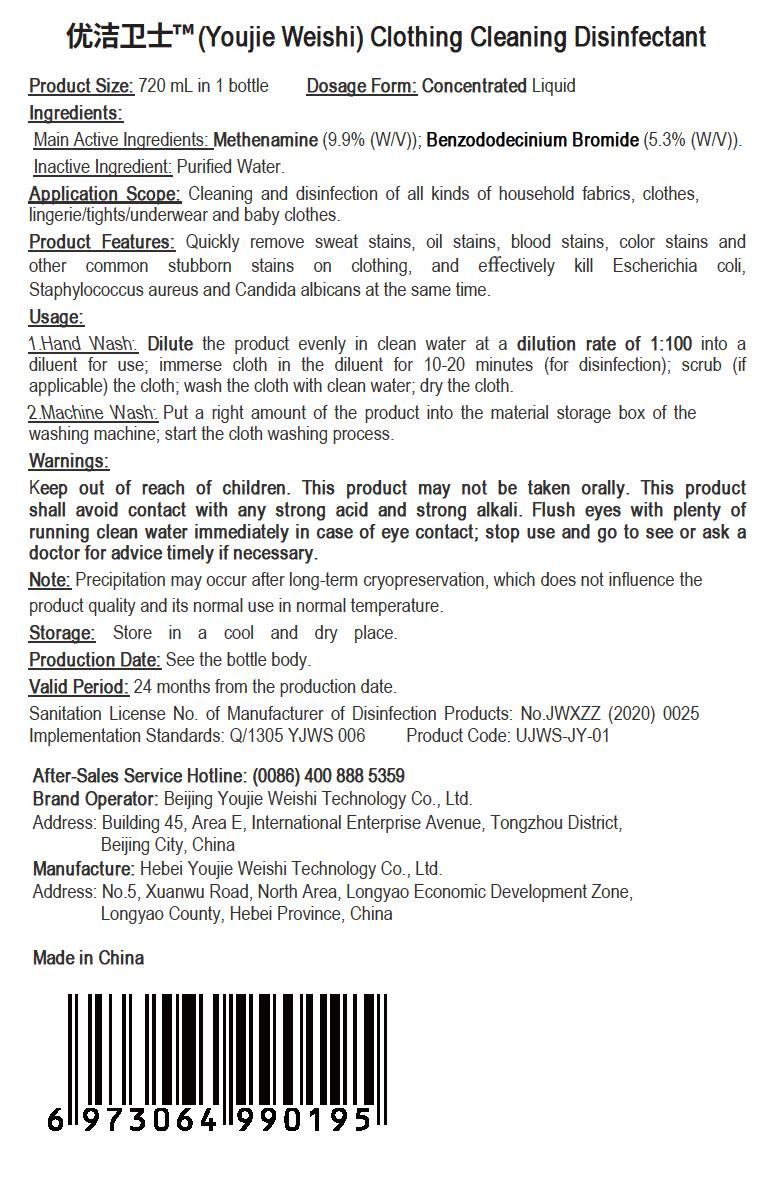 DRUG LABEL: Youjie Weishi Cloth Cleaning Disinfectant
NDC: 55455-008 | Form: LIQUID
Manufacturer: Hebei Youjie Weishi Technology Co., Ltd.
Category: otc | Type: HUMAN OTC DRUG LABEL
Date: 20200507

ACTIVE INGREDIENTS: BENZODODECINIUM BROMIDE 38.16 g/720 mL; METHENAMINE 71.28 g/720 mL
INACTIVE INGREDIENTS: WATER

PURPOSE

Disinfection
Sterilization
No Rinseing

INACTIVE INGREDIENT

water

DOSAGE AND ADMINISTRATION

This product shall be stored in a cool, dry place.

ACTIVE INGREDIENT

Hexamethylenetetramine

Benzalkonium Bromide

keep out of reach of children

INDICATIONS AND USAGE

1 .Hand Wash; Dilute the product evenly in clean water at a diution rate of 1:100 into a diluent for use; immerse cloth in the diluent for 10-20 minutes (for disinfection); scrub (if applicable) the cloth; wash the cloth with clean water, dry the cloth.
2. Machine Wash. Put a right amount of the product into the material storage box of the washing machine, start the cloth washing process.

WARNINGS

This product is a disinfectant for external use, and may not be taken orally; it must be kept out of reach of children. This product shall avoid contact with any detergent and antagonist drug. This product cannot be used together with peroxide.